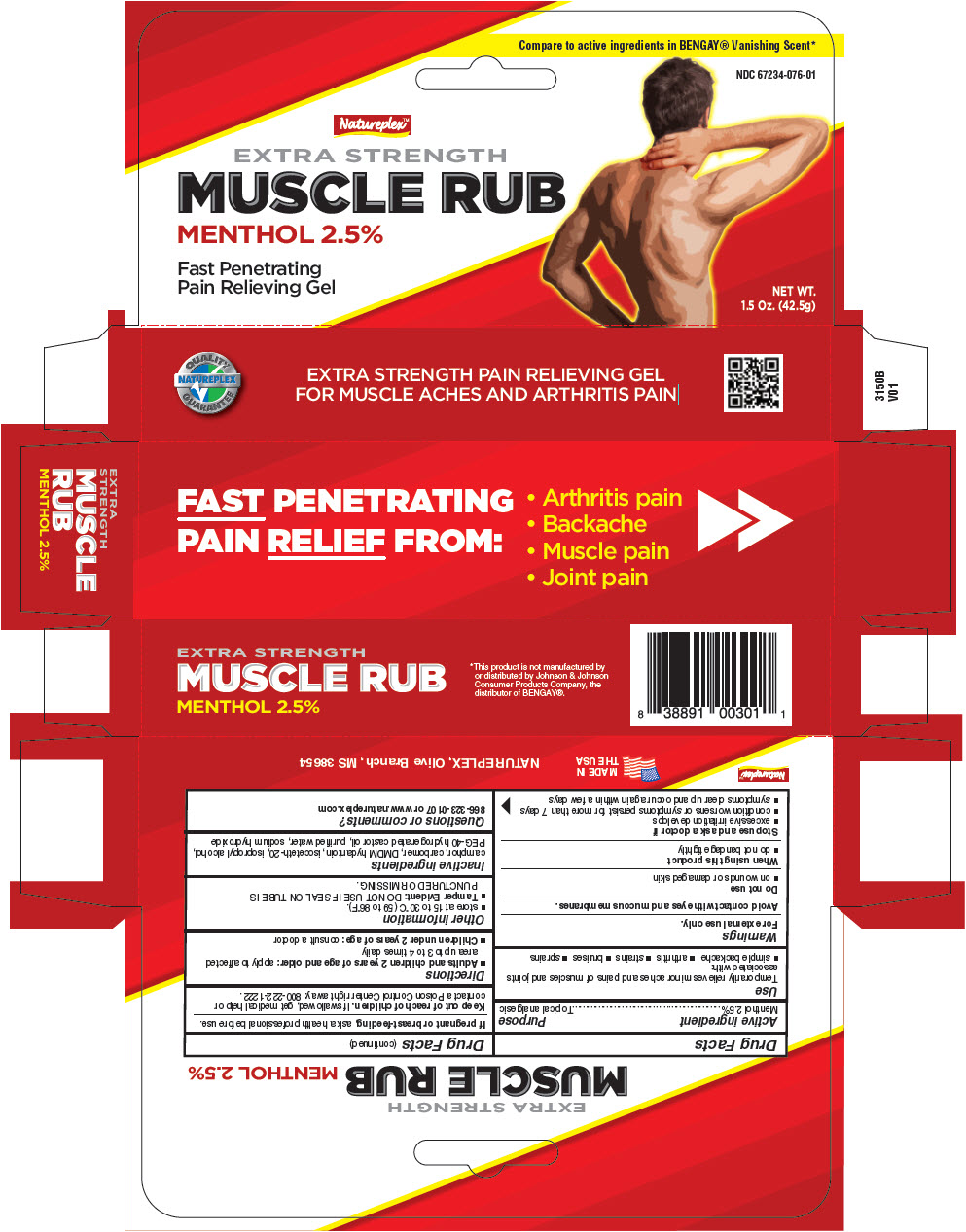 DRUG LABEL: NATUREPLEX EXTRA STRENGTH MUSCLE RUB
NDC: 67234-076 | Form: CREAM
Manufacturer: Natureplex LLC
Category: otc | Type: HUMAN OTC DRUG LABEL
Date: 20241231

ACTIVE INGREDIENTS: MENTHOL, UNSPECIFIED FORM 2.5 g/100 g
INACTIVE INGREDIENTS: CAMPHOR (SYNTHETIC); CARBOMER HOMOPOLYMER, UNSPECIFIED TYPE; DMDM HYDANTOIN; ISOCETETH-20; ISOPROPYL ALCOHOL; POLYOXYL 40 HYDROGENATED CASTOR OIL; WATER

NATUREPLEX™ EXTRA STRENGTH MUSCLE RUB

Drug Facts

Active ingredient

Menthol 2.5%

Purpose

Topical analgesic

Use

Temporarily relieves minor aches and pains of muscles and joints associated with:

- simple backache
- arthritis
- strains
- bruises
- sprains

Warnings

For external use only.

Avoid contact with eyes and mucous membranes.

Do not use

- on wounds or damaged skin

When using this product

- do not bandage tightly

Stop use and ask a doctor if

- excessive irritation develops
- condition worsens or symptoms persist for more than 7 days
- symptoms clear up and occur again within a few days

PREGNANCY OR BREAST FEEDING

If pregnant or breast-feeding, ask a health professional before use.

Keep out of reach of children. If swallowed, get medical help or contact a Poison Control Center right away: 800-222-1222.

Directions

- Adults and children 2 years of age and older: apply to affected area up to 3 to 4 times daily
- Children under 2 years of age: consult a doctor

Other information

- store at 15 to 30°C (59 to 86°F).
- Tamper Evident: DO NOT USE IF SEAL ON TUBE IS PUNCTURED OR MISSING.

Inactive ingredients

camphor, carbomer, DMDM hydantoin, isoceteth-20, isopropyl alcohol, PEG-40 hydrogenated castor oil, purified water, sodium hydroxide

Questions or comments?

866-323-0107 or www.natureplex.com

PRINCIPAL DISPLAY PANEL - 42.5 g Tube Carton

FAST PENETRATING
PAIN RELIEF FROM:

- Arthritis pain
- Backache
- Muscle pain
- Joint pain